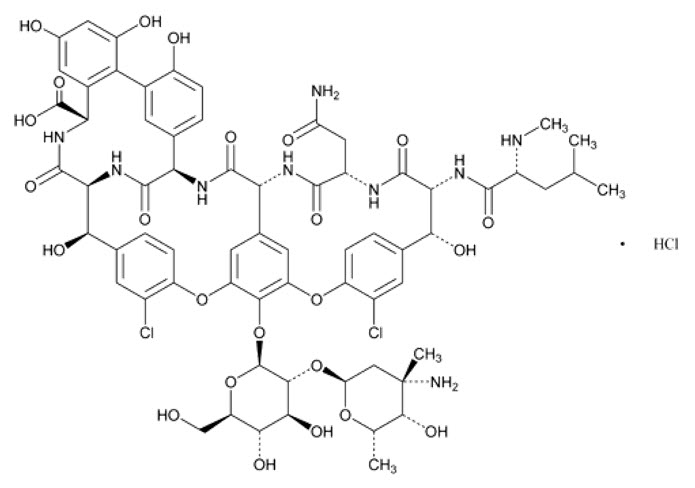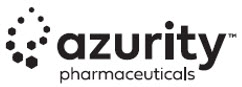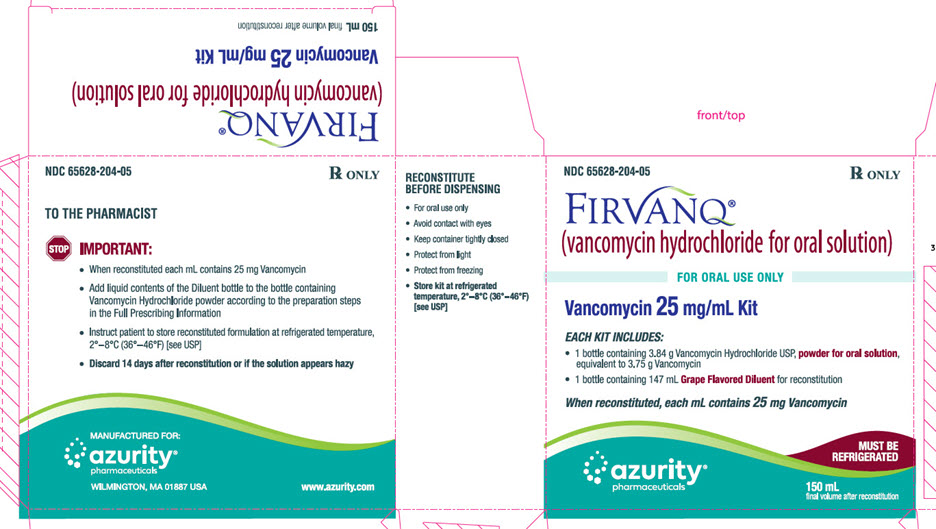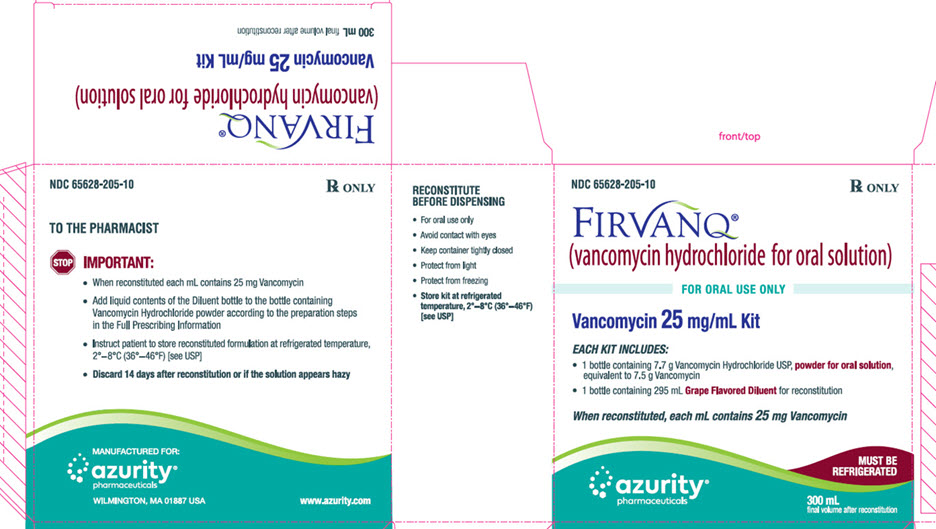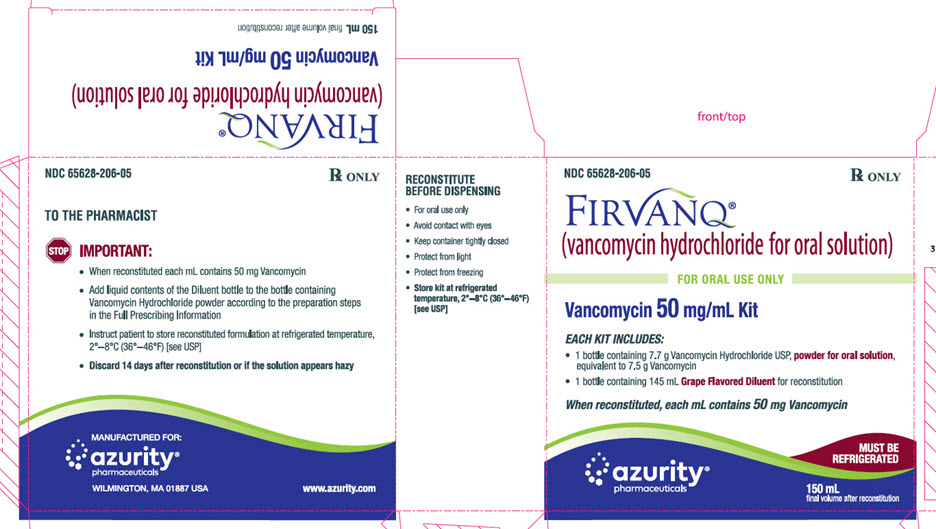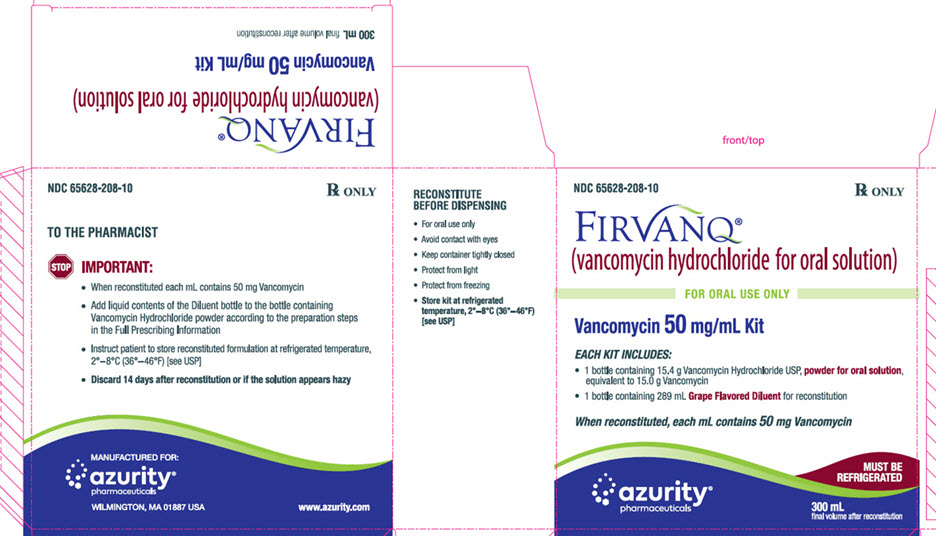 DRUG LABEL: FIRVANQ
NDC: 65628-204 | Form: KIT | Route: ORAL
Manufacturer: Azurity Pharmaceuticals, Inc
Category: prescription | Type: HUMAN PRESCRIPTION DRUG LABEL
Date: 20251215

ACTIVE INGREDIENTS: VANCOMYCIN HYDROCHLORIDE 1 g/1 g
INACTIVE INGREDIENTS: ANHYDROUS CITRIC ACID; D&C YELLOW NO. 10; FD&C RED NO. 40; WATER; SODIUM BENZOATE; SUCRALOSE

HIGHLIGHTS OF PRESCRIBING INFORMATION

These highlights do not include all the information needed to use FIRVANQ®safely and effectively. See Full Prescribing Information for FIRVANQ®.
FIRVANQ (vancomycin hydrochloride for oral solution)
Initial U.S. Approval: 1964

1 INDICATIONS AND USAGE

FIRVANQ is a glycopeptide antibacterial indicated in adults and pediatric patients less than 18 years of age for the treatment of: (1)

- Clostridium difficile‑associated diarrhea
- Enterocolitis caused by Staphylococcus aureus(including methicillin‑resistant strains)

Important Limitations of Use: (1) (5.1)

- Orally administered vancomycin hydrochloride is not effective for treatment of other types of infections.

To reduce the development of drug‑resistant bacteria and maintain the effectiveness of FIRVANQ and other antibacterial drugs, FIRVANQ should be used only to treat or prevent infections that are proven or strongly suspected to be caused by bacteria. (1)

2 DOSAGE AND ADMINISTRATION

- C. difficile‑associated diarrhea:
  - Adult Patients (18 years of age and older): 125 mg orally 4 times daily for 10 days. (2.2)
  - Pediatric Patients (less than 18 years of age): 40 mg/kg in 3 or 4 divided doses for 7 to 10 days. The total daily dosage should not exceed 2 g. (2.3)
- Staphylococcal enterocolitis:
  - Adult Patients (18 years of age and older): 500 mg to 2 g orally in 3 or 4 divided doses for 7 to 10 days. (2.2)
  - Pediatric Patients (less than 18 years of age): 40 mg/kg in 3 or 4 divided doses for 7 to 10 days. The total daily dosage should not exceed 2 g. (2.3)
- See Full Prescribing Information for preparation and important administration information. (2.1)

3 DOSAGE FORMS AND STRENGTHS

Each FIRVANQ kit contains: vancomycin hydrochloride USP, powder for oral solution, equivalent to 3.75 g, 7.5 g or 15.0 g vancomycin, and Grape‑Flavored Diluent. (3)

4 CONTRAINDICATIONS

Hypersensitivity to vancomycin (4)

5 WARNINGS AND PRECAUTIONS

- FIRVANQ must be given orally for treatment of C. difficile‑associated diarrhea and staphylococcal enterocolitis. Orally administered vancomycin hydrochloride is not effective for treatment of other types of infections. (5.1)
- Clinically significant serum concentrations have been reported in some patients who have taken multiple oral doses of vancomycin hydrochloride for C. difficile‑associated diarrhea. Monitoring of serum concentrations may be appropriate in some instances. (5.2)
- Nephrotoxicity has occurred following oral vancomycin hydrochloride therapy and can occur either during or after completion of therapy. The risk is increased in geriatric patients. Monitor renal function. (5.3)
- Ototoxicity has occurred in patients receiving vancomycin hydrochloride. Assessment of auditory function may be appropriate in some instances. (5.4)
- Severe Dermatologic Reactions: Discontinue FIRVANQ at the first appearance of skin rashes, mucosal lesions, or blisters. (5.5)
- Prescribing FIRVANQ in the absence of a proven or strongly suspected bacterial infection is unlikely to provide benefit to the patient and increases the risk of the development of drug-resistant bacteria. (5.7)

6 ADVERSE REACTIONS

The most common adverse reactions (≥ 10%) were nausea (17%), abdominal pain (15%), and hypokalemia (13%). (6.1)

To report SUSPECTED ADVERSE REACTIONS, contact Azurity Pharmaceuticals, Inc. at 1‑855-379-0383, or FDA at 1-800-FDA-1088 or www.fda.gov/medwatch.

8 USE IN SPECIFIC POPULATIONS

Geriatrics: In patients over 65 years of age, including those with normal renal function prior to treatment, renal function should be monitored during and following treatment with vancomycin hydrochloride to detect potential vancomycin induced nephrotoxicity. (5.3) (6.1) (8.5) (14.1)

FULL PRESCRIBING INFORMATION

1 INDICATIONS AND USAGE

FIRVANQ is indicated for the treatment of Clostridium difficile‑associated diarrhea in adults and pediatric patients less than 18 years of age.

FIRVANQ is also indicated for the treatment of enterocolitis caused by Staphylococcus aureus(including methicillin‑resistant strains) in adults and pediatric patients less than 18 years of age.

Important Limitations of Use

- Parenteral administration of vancomycin is not effective for the above infections; therefore, vancomycin must be given orally for these infections.
- Orally administered vancomycin hydrochloride is not effective for treatment of other types of infections.

To reduce the development of drug‑resistant bacteria and maintain the effectiveness of FIRVANQ and other antibacterial drugs, FIRVANQ should be used only to treat or prevent infections that are proven or strongly suspected to be caused by susceptible bacteria. When culture and susceptibility information are available, they should be considered in selecting or modifying antibacterial therapy. In the absence of such data, local epidemiology and susceptibility patterns may contribute to the empiric selection of therapy.

2 DOSAGE AND ADMINISTRATION

2.1 Important Administration Instructions

Prior to oral administration, the supplied FIRVANQ powder must be reconstituted by the healthcare provider (i.e., a pharmacist) to produce the oral solution [ see Dosage and Administration (2.4) ].

2.2 Adults

- C. difficile‑associated diarrhea: The recommended dose is 125 mg administered orally 4 times daily for 10 days.
- Staphylococcal enterocolitis: Total daily dosage is 500 mg to 2 g administered orally in 3 or 4 divided doses for 7 to 10 days.

2.3 Pediatric Patients (less than 18 years of age)

For both C. difficile‑associated diarrhea and staphylococcal enterocolitis, the usual daily dosage of FIRVANQ is 40 mg/kg in 3 or 4 divided doses for 7 to 10 days. The total daily dosage should not exceed 2 g.

2.4 Preparation and Storage of Solutions of FIRVANQ

Each FIRVANQ kit contains 1 bottle of vancomycin hydrochloride USP powder and 1 bottle of pre‑measured Grape‑Flavored Diluent to be added to the vancomycin bottle. A healthcare provider (i.e., a pharmacist) must reconstitute vancomycin hydrochloride USP powder with the Grape‑Flavored Diluent provided in the kit. FIRVANQ is available in various strengths and volumes in the kit as shown in Table 1.

Table 1: Vancomycin Concentration and Volume after Reconstitution
Vancomycin Concentration after Reconstitution | Final Volume of FIRVANQ after Reconstitution | Vancomycin Strength per Bottle | Diluent for FIRVANQ
25 mg/mL | 150 mL | 3.75 g | 147 mL
 | 300 mL | 7.5 g | 295 mL
50 mg/mL | 150 mL | 7.5 g | 145 mL
 | 300 mL | 15.0 g | 289 mL

Steps for the Preparation of Solutions of FIRVANQ

1. Hold the neck of the bottle containing the vancomycin hydrochloride USP powder for oral solution (see Table 1), and tap the bottom edges on a hard surface to loosen the powder.
2. Remove the cap from the vancomycin hydrochloride USP powder for oral solution bottle (“Powder Bottle”).
3. Tap the top of the induction seal liner to loosen any powder that may have adhered to the liner.
4. Carefully and slowly peel back the inner foil seal liner from the Powder Bottle.
5. Shake the Grape‑Flavored Diluent (see Table 1) for a few seconds.
6. Remove the cap from the diluent bottle.
7. Carefully and slowly peel back the inner foil seal from the diluent bottle.
8. Transfer approximately one-half the contents of Grape-Flavored Diluent into the Powder Bottle.
9. Replace the Powder Bottle cap, tighten onto the Powder Bottle, and shake the Powder Bottle vertically for approximately 45 seconds. NOTE: DO NOT use the diluent cap on the Powder Bottle as it may cause the solution to leak from the bottle.
10. Re-open the Powder Bottle and add the remaining Grape‑Flavored Diluent into the Powder Bottle.
11. Replace the Powder Bottle cap, tighten onto the Powder Bottle, and shake the Powder Bottle for approximately 30 seconds. NOTE: DO NOT use the diluent cap on the Powder Bottle as it may cause the solution to leak from the bottle.
12. Dispense the Powder Bottle containing reconstituted solution of FIRVANQ oral solution to the patient [ see Patient Counseling Information (17) ].
13. Instruct the patient to shake the reconstituted solution of FIRVANQ well before each use and to use an oral dosing device that measures the appropriate volume of the oral solution in milliliters.
14. Store the reconstituted solution of FIRVANQ at refrigerated conditions, 2°C to 8°C (36°F to 46°F) when not in use.
15. Discard the reconstituted solution of FIRVANQ after 14 days, or if it appears hazy or contains particulates.

3 DOSAGE FORMS AND STRENGTHS

Each FIRVANQ kit contains vancomycin hydrochloride USP as white to almost white or tan to brown powder for oral solution, equivalent to 3.75 g, 7.5 g or 15.0 g vancomycin, and Grape‑Flavored Diluent for reconstitution.

4 CONTRAINDICATIONS

FIRVANQ is contraindicated in patients with known hypersensitivity to vancomycin.

5 WARNINGS AND PRECAUTIONS

5.1 Oral Use Only

FIRVANQ must be given orally for treatment of C. difficile‑associated diarrhea and staphylococcal enterocolitis. Orally administered vancomycin is not effective for treatment of other types of infections.

Parenteral administration of vancomycin is noteffective for treatment of C. difficile‑associated diarrhea and staphylococcal enterocolitis. If parenteral vancomycin therapy is desired, use an intravenous preparation of vancomycin and consult the Full Prescribing Information accompanying that preparation.

5.2 Potential for Systemic Absorption

Significant systemic absorption has been reported in some patients (e.g., patients with renal insufficiency and/or colitis) who have taken multiple oral doses of vancomycin hydrochloride for C. difficile‑associated diarrhea. In these patients, serum vancomycin concentrations reached therapeutic levels for the treatment of systemic infections. Some patients with inflammatory disorders of the intestinal mucosa also may have significant systemic absorption of vancomycin. These patients may be at risk for the development of adverse reactions associated with higher doses of FIRVANQ; therefore, monitoring of serum concentrations of vancomycin may be appropriate in some instances, e.g., in patients with renal insufficiency and/or colitis or in those receiving concomitant therapy with an aminoglycoside antibacterial drug.

5.3 Nephrotoxicity

Nephrotoxicity (e.g., reports of renal failure, renal impairment, blood creatinine increased) has occurred following oral vancomycin hydrochloride therapy in randomized controlled clinical trials and can occur either during or after completion of therapy. The risk of nephrotoxicity is increased in patients over 65 years of age [ see Adverse Reactions (6.1) and Use in Specific Populations (8.5) ].

In patients over 65 years of age, including those with normal renal function prior to treatment, renal function should be monitored during and following treatment with FIRVANQ to detect potential vancomycin- induced nephrotoxicity.

5.4 Ototoxicity

Ototoxicity has occurred in patients receiving vancomycin. It may be transient or permanent. It has been reported mostly in patients who have been given high intravenous doses, who have an underlying hearing loss, or who are receiving concomitant therapy with another ototoxic agent, such as an aminoglycoside. Serial tests of auditory function may be helpful in order to minimize the risk of ototoxicity [ see Adverse Reactions (6.2) ].

5.5 Severe Dermatologic Reactions

Severe dermatologic reactions such as toxic epidermal necrolysis (TEN), Stevens-Johnson syndrome (SJS), drug reaction with eosinophilia and systemic symptoms (DRESS), acute generalized exanthematous pustulosis (AGEP), and linear lgA bullous dermatosis (LABD) have been reported in association with the use of vancomycin. Cutaneous signs or symptoms reported include skin rashes, mucosal lesions, and blisters. Discontinue FIRVANQ at the first appearance of signs and symptoms of TEN, SJS, DRESS, AGEP, or LABD.

5.6 Potential for Microbial Overgrowth

Use of FIRVANQ may result in the overgrowth of non‑susceptible bacteria. If superinfection occurs during therapy, appropriate measures should be taken.

5.7 Development of Drug-Resistant Bacteria

Prescribing FIRVANQ in the absence of a proven or strongly suspected bacterial infection or a prophylactic indication is unlikely to provide benefit to the patient and increases the risk of the development of drug‑resistant bacteria.

5.8 Hemorrhagic Occlusive Retinal Vasculitis (HORV)

Hemorrhagic occlusive retinal vasculitis, including permanent loss of vision, occurred in patients receiving intracameral or intravitreal administration of vancomycin during or after cataract surgery. The safety and efficacy of vancomycin administered by the intracameral or intravitreal route have not been established by adequate and well‑controlled studies. Vancomycin is not indicated for prophylaxis of endophthalmitis.

6 ADVERSE REACTIONS

6.1 Clinical Trials Experience

Because clinical studies are conducted under widely varying conditions, adverse reaction rates observed in the clinical studies of a drug cannot be directly compared to rates in the clinical studies of another drug and may not reflect the rates observed in practice.

The data described below reflect exposure to vancomycin hydrochloride in 260 adult subjects in two Phase 3 clinical trials for the treatment of C. difficile‑associated diarrhea. In both trials, subjects received vancomycin hydrochloride 125 mg orally four times daily. The mean duration of treatment was 9.4 days. The median age of patients was 67, ranging between 19 and 96 years of age. Patients were predominantly Caucasian (93%), and 52% were male.

Adverse reactions occurring in ≥ 5% of vancomycin hydrochloride‑treated subjects are shown in Table 2. The most common adverse reactions associated with vancomycin hydrochloride (≥ 10%) were nausea, abdominal pain, and hypokalemia.

Table 2: Common (≥ 5%) Adverse Reactions* for Vancomycin Hydrochloride Reported in Clinical Trials for Treatment of C. difficile Associated Diarrhea
System/Organ Class | Adverse Reaction | Vancomycin Hydrochloride (%) (N=260)
Gastrointestinal disorders | Nausea | 17
Gastrointestinal disorders | Abdominal pain | 15
Gastrointestinal disorders | Vomiting | 9
Gastrointestinal disorders | Diarrhea | 9
Gastrointestinal disorders | Flatulence | 8
General disorders and administration site conditions | Pyrexia | 9
General disorders and administration site conditions | Edema peripheral | 6
General disorders and administration site conditions | Fatigue | 5
Infections and infestations | Urinary tract infection | 8
Metabolism and nutrition disorders | Hypokalemia | 13
Musculoskeletal and connective tissue disorders | Back pain | 6
Nervous system disorders | Headache | 7
* Adverse reaction rates were derived from the incidence of treatment‑emergent adverse events.

Nephrotoxicity (e.g., reports of renal failure, renal impairment, blood creatinine increased) occurred in 5% of subjects treated with vancomycin hydrochloride. Nephrotoxicity following vancomycin hydrochloride typically first occurred within one week after completion of treatment (median day of onset was Day 16). Nephrotoxicity following vancomycin hydrochloride occurred in 6% of subjects over 65 years of age and 3% of subjects 65 years of age and younger [ see Warnings and Precautions (5.3) ]. Nephrotoxicity can also occur during oral vancomycin administration.

The incidences of hypokalemia, urinary tract infection, peripheral edema, insomnia, constipation, anemia, depression, vomiting, and hypotension were higher among subjects over 65 years of age than in subjects 65 years of age and younger [ see Use in Specific Populations (8.5) ].

Discontinuation of study drug due to adverse events occurred in 7% of subjects treated with vancomycin hydrochloride. The most common adverse events leading to discontinuation of vancomycin hydrochloride were C. difficilecolitis (< 1%), nausea (< 1%), and vomiting (< 1%).

6.2 Postmarketing Experience

The following adverse reactions have been identified during post‑approval use of vancomycin hydrochloride. Because these reactions are reported voluntarily from a population of uncertain size, it is not always possible to reliably estimate their frequency or establish a causal relationship to drug exposure.

Ototoxicity: Cases of hearing loss associated with intravenously administered vancomycin have been reported. Most of these patients had kidney dysfunction or a preexisting hearing loss or were receiving concomitant treatment with an ototoxic drug [ see Warnings and Precautions (5.4) ]. Vertigo, dizziness, and tinnitus have been reported.

Skin and Subcutaneous Tissue Disorders:Severe dermatologic reactions such as toxic epidermal necrolysis (TEN), Stevens-Johnson syndrome (SJS), drug reaction with eosinophilia and systemic symptoms (DRESS), acute generalized exanthematous pustulosis (AGEP), and linear lgA bullous dermatosis (LABD) [ see Warnings and Precautions (5.5) ], rashes (including exfoliative dermatitis).

Hematopoietic: Reversible neutropenia, usually starting 1 week or more after onset of intravenous therapy with vancomycin or after a total dose of more than 25 g, has been reported. Neutropenia appears to be promptly reversible when vancomycin is discontinued. Thrombocytopenia has been reported.

Miscellaneous: Anaphylaxis, drug fever, chills, nausea, eosinophilia, and vasculitis have been reported with the administration of vancomycin.

A condition has been reported with oral vancomycin that is similar to the IV–induced syndrome with symptoms consistent with anaphylactoid reactions, including hypotension, wheezing, dyspnea, urticaria, pruritus, flushing of the upper body (“vancomycin infusion reaction”), pain and muscle spasm of the chest and back. These reactions usually resolve within 20 minutes but may persist for several hours.

7 DRUG INTERACTIONS

No drug interaction studies have been conducted using orally administered vancomycin hydrochloride products.

8 USE IN SPECIFIC POPULATIONS

8.1 Pregnancy

Risk Summary

There are no available data on FIRVANQ use in pregnant women to inform a drug-associated risk of major birth defects or miscarriage. Available published data on vancomycin use in pregnancy during the second and third trimesters have not shown an association with adverse pregnancy-related outcomes (see Data) . Vancomycin did not show adverse developmental effects when administered intravenously to pregnant rats and rabbits during organogenesis at doses less than or equal to the recommended maximum human dose based on body surface area (see Data) .

All pregnancies have a background risk of birth defect, loss or other adverse outcomes. In the U.S. general population, the estimated background risk of major birth defects and miscarriage in clinically recognized pregnancies is 2 to 4% and 15 to 20%, respectively.

Data

Human Data

A published study evaluated hearing loss and nephrotoxicity in infants of pregnant intravenous drug users treated with vancomycin for suspected or documented methicillin‑resistant S. aureusin the second or third trimester. The comparison groups were 10 non‑intravenous drug‑dependent patients who received no treatment, and 10 untreated intravenous drug‑dependent patients served as substance abuse controls. No infant in the vancomycin-exposed group had abnormal sensorineural hearing at 3 months of age or nephrotoxicity.

A published prospective study assessed outcomes in 55 pregnant women with a positive Group B Streptococcusculture and a high‑risk penicillin allergy with resistance to clindamycin or unknown sensitivity who were administered vancomycin at the time of delivery. Vancomycin dosing ranged from the standard 1 g intravenously every 12 hours to 20 mg/kg intravenous every 8 hours (maximum individual dose 2 g). No major adverse reactions were recorded either in the mothers or their newborns. None of the newborns had sensorineural hearing loss. Neonatal renal function was not examined, but all of the newborns were discharged in good condition.

Animal Data

Vancomycin did not cause fetal malformations when administered during organogenesis to pregnant rats (gestation days 6 to 15) and rabbits (gestation days 6 to 18) at the equivalent recommended maximum human dose (based on body surface area comparisons) of 200 mg/kg/day IV to rats or 120 mg/kg/day IV to rabbits. No effects on fetal weight or development were seen in rats at the highest dose tested or in rabbits given 80 mg/kg/day (approximately 1 and 0.8 times the recommended maximum human dose based on body surface area, respectively). Maternal toxicity was observed in rats (at doses 120 mg/kg and above) and rabbits (at 80 mg/kg and above).

8.2 Lactation

Risk Summary

There are insufficient data to inform the levels of vancomycin in human milk. However, systemic absorption of vancomycin following oral administration is expected to be minimal [ see Clinical Pharmacology (12.3) ]. There are no data on the effects of FIRVANQ on the breastfed infant or milk production. The developmental and health benefits of breastfeeding should be considered along with the mother’s clinical need for FIRVANQ and any potential adverse effects on the breastfed infant from FIRVANQ or from the underlying maternal condition.

8.4 Pediatric Use

FIRVANQ is indicated in pediatric patients less than 18 years of age for the treatment of C. difficile‑associated diarrhea and enterocolitis caused by S. aureus(including methicillin‑resistant strains) [ see Indications and Usage (1) and Dosage and Administration (2.3) ].

8.5 Geriatric Use

In clinical trials, 54% of vancomycin hydrochloride‑treated subjects were > 65 years of age. Of these, 40% were between the ages of > 65 and 75, and 60% were > 75 years of age.

Clinical studies with vancomycin hydrochloride in C. difficile‑associated diarrhea have demonstrated that geriatric subjects are at increased risk of developing nephrotoxicity following treatment with oral vancomycin hydrochloride, which may occur during or after completion of therapy. In patients over 65 years of age, including those with normal renal function prior to treatment, renal function should be monitored during and following treatment with vancomycin hydrochloride to detect potential vancomycin-induced nephrotoxicity [ see Warnings and Precautions(5.3), Adverse Reactions (6.1) and Clinical Studies (14.1) ].

Patients over 65 years of age may take longer to respond to therapy compared to patients 65 years of age and younger [ see Clinical Studies (14.1) ]. Clinicians should be aware of the importance of appropriate duration of vancomycin hydrochloride treatment in patients over 65 years of age and not discontinue or switch to alternative treatment prematurely.

10 OVERDOSAGE

Supportive care is advised, with maintenance of glomerular filtration. Vancomycin is poorly removed by dialysis. Hemofiltration and hemoperfusion with polysulfone resin have been reported to result in increased vancomycin clearance.

For current information on the management of overdosage, contact the National Poison Control Center at 1‑800‑222‑1222 or www.poison.org.

11 DESCRIPTION

FIRVANQ for oral administration contains the hydrochloride salt of vancomycin, a tricyclic glycopeptide antibiotic derived from Amycolatopsis orientalis(formerly Nocardia orientalis), which has the chemical formula C66H75Cl2N9O24•HCl. The molecular weight of vancomycin hydrochloride is 1485.71 g/mol.

Vancomycin hydrochloride has the structural formula:

Each FIRVANQ kit contains a bottle of vancomycin hydrochloride USP, as white to almost white or tan to brown powder for oral solution, and a bottle of pre‑measured Grape‑Flavored Diluent, in the strengths and volumes listed in Table 3.

Table 3: Vancomycin Strength, Diluent Volume and Vancomycin Concentration after Reconstitution
Vancomycin Strength per Bottle | Equivalent Amount of Vancomycin Hydrochloride per Bottle | Diluent Volume for FIRVANQ | Vancomycin Concentration after Reconstitution
3.75 g | 3.84 g | 147 mL | 25 mg/mL
7.5 g | 7.7 g | 295 mL
7.5 g | 7.7 g | 145 mL | 50 mg/mL
15.0 g | 15.4 g | 289 mL

The Grape‑Flavored Diluent used to reconstitute the oral solution contains: artificial grape flavor, citric acid (anhydrous), D&C Yellow No. 10, FD&C Red No. 40, purified water, sodium benzoate and sucralose.

12 CLINICAL PHARMACOLOGY

12.1 Mechanism of Action

Vancomycin is an antibacterial drug [ see Microbiology (12.4) ].

12.3 Pharmacokinetics

Vancomycin is poorly absorbed after oral administration. During multiple dosing of vancomycin hydrochloride capsules at 250 mg every 8 hours for 7 doses, fecal concentrations of vancomycin in volunteers exceeded 100 mcg/g in the majority of samples. No blood concentrations were detected and urinary recovery did not exceed 0.76%. In anephric subjects with no inflammatory bowel disease who received vancomycin oral solution 2 g for 16 days, blood concentrations of vancomycin were ≤ 0.66 mcg/mL in 2 of 5 subjects. No measurable blood concentrations were attained in the other 3 subjects. Following doses of 2 g daily, concentrations of drug were > 3100 mcg/g in the feces and < 1 mcg/mL in the serum of subjects with normal renal function who had C. difficile‑associated diarrhea. After multiple‑dose oral administration of vancomycin, measurable serum concentrations may occur in patients with active C. difficile‑associated diarrhea, and, in the presence of renal impairment, the possibility of accumulation exists. It should be noted that the total systemic and renal clearances of vancomycin are reduced in the elderly [ see Use in Specific Populations (8.5) ].

12.4 Microbiology

Mechanism of Action

The bactericidal action of vancomycin against the vegetative cells of C. difficileand S. aureusresults primarily from inhibition of cell‑wall biosynthesis. In addition, vancomycin alters bacterial‑cell‑membrane permeability and RNA synthesis.

Mechanism of Resistance

C. difficile

Isolates of C. difficilegenerally have vancomycin minimal inhibitory concentrations (MICs) of < 1 mcg/mL; however, vancomycin MICs ranging from 4 mcg/mL to 16 mcg/mL have been reported. The mechanism which mediates C. difficile's decreased susceptibility to vancomycin has not been fully elucidated.

S. aureus

S. aureusisolates with vancomycin MICs as high as 1024 mcg/mL have been reported. The exact mechanism of this resistance is not clear but is believed to be due to cell wall thickening and potentially the transfer of genetic material.

Vancomycin has been shown to be active against susceptible isolates of the following bacteria in clinical infections [ see Indications and Usage (1) ].

Anaerobic gram‑positive bacteria
C. difficileisolates associated with C. difficile‑associated diarrhea.

Gram‑positive bacteria
S. aureus(including methicillin‑resistant isolates) associated with enterocolitis.

13 NONCLINICAL TOXICOLOGY

13.1 Carcinogenesis, Mutagenesis, Impairment of Fertility

No long‑term carcinogenesis studies in animals have been conducted.

At concentrations up to 1000 mcg/mL, vancomycin had no mutagenic effect in vitroin the mouse lymphoma forward mutation assay or the primary rat hepatocyte unscheduled DNA synthesis assay. The concentrations tested in vitrowere above the peak plasma vancomycin concentrations of 20 to 40 mcg/mL usually achieved in humans after slow infusion of the maximum recommended dose of 1 g. Vancomycin had no mutagenic effect in vivoin the Chinese hamster sister chromatid exchange assay (400 mg/kg IP) or the mouse micronucleus assay (800 mg/kg IP).

No definitive fertility studies have been conducted.

14 CLINICAL STUDIES

14.1 Diarrhea Associated with Clostridium difficile

In two trials, vancomycin hydrochloride 125 mg orally four times daily for 10 days was evaluated in 266 adult subjects with C. difficile‑associated diarrhea (CDAD). Enrolled subjects were 18 years of age or older and received no more than 48 hours of treatment with oral vancomycin hydrochloride or oral/intravenous metronidazole in the 5 days preceding enrollment. CDAD was defined as ≥ 3 loose or watery bowel movements within the 24 hours preceding enrollment, and the presence of either C. difficiletoxin A or B, or pseudomembranes on endoscopy within the 72 hours preceding enrollment. Subjects with fulminant C. difficiledisease, sepsis with hypotension, ileus, peritoneal signs or severe hepatic disease were excluded.

Efficacy analyses were performed on the Full Analysis Set (FAS), which included randomized subjects who received at least one dose of vancomycin hydrochloride and had any post‑dosing investigator evaluation data (N = 259; 134 in Trial 1 and 125 in Trial 2).

The demographic profile and baseline CDAD characteristics of enrolled subjects were similar in the two trials. Vancomycin hydrochloride‑treated subjects had a median age of 67 years, were mainly white (93%), and male (52%). CDAD was classified as severe (defined as 10 or more unformed bowel movements per day or white blood cell count (WBC) ≥ 15000/mm^3) in 25% of subjects, and 47% were previously treated for CDAD.

Efficacy was assessed by using clinical success, defined as diarrhea resolution and the absence of severe abdominal discomfort due to CDAD, on Day 10. An additional efficacy endpoint was the time to resolution of diarrhea, defined as the beginning of diarrhea resolution that was sustained through the end of the prescribed active treatment period.

The results for clinical success for vancomycin hydrochloride‑treated subjects in both trials are shown in Table 4.

Table 4: Clinical Success Rates (Full Analysis Set)
 | Clinical Success Rate Vancomycin Hydrochloride % (N) | 95% Confidence Interval
Trial 1 | 81.3 (134) | (74.4, 88.3)
Trial 2 | 80.8 (125) | (73.5, 88.1)

The median time to resolution of diarrhea was 5 days and 4 days in Trial 1 and Trial 2, respectively. For subjects older than 65 years of age, the median time to resolution was 6 days and 4 days in Trial 1 and Trial 2, respectively. In subjects with diarrhea resolution at end‑of‑treatment with vancomycin hydrochloride, recurrence of CDAD during the following four weeks occurred in 25 of 107 (23%) and 18 of 102 (18%) in Trial 1 and Trial 2, respectively.

Restriction Endonuclease Analysis (REA) was used to identify C. difficilebaseline isolates in the BI group. In Trial 1, the vancomycin hydrochloride‑treated subjects were classified at baseline as follows: 31 (23%) with BI strain, 69 (52%) with non‑BI strain, and 34 (25%) with unknown strain. Clinical success rates were 87% for BI strain, 81% for non‑BI strain, and 76% for unknown strain. In subjects with diarrhea resolution at end‑of‑treatment with vancomycin hydrochloride, recurrence of CDAD during the following four weeks occurred in 7 of 26 subjects with BI strain, 12 of 56 subjects with non‑BI strain, and 6 of 25 subjects with unknown strain.

16 HOW SUPPLIED/STORAGE AND HANDLING

How Supplied

Each FIRVANQ kit contains a bottle of vancomycin hydrochloride USP, as white to almost white or tan to brown powder for oral solution, and a bottle of pre‑measured Grape‑Flavored Diluent, in the strengths and volumes listed in Table 5.

Table 5: Vancomycin Strength, Diluent Volume and National Drug Code (NDC) Numbers
Vancomycin Strength per Bottle | Diluent Volume for FIRVANQ | NDC Numbers
3.75 g | 147 mL | 65628‑204‑05
7.5 g | 295 mL | 65628‑205‑10
7.5 g | 145 mL | 65628‑206‑05
15.0 g | 289 mL | 65628‑208‑10

Storage and Handling

Store the FIRVANQ kit at refrigerated conditions, 2°C to 8°C (36°F to 46°F).

Store reconstituted solutions of FIRVANQ at 2°C to 8°C [ see Dosage and Administration (2.4) ].

Do not freeze. Keep container tightly closed. Protect from light.

17 PATIENT COUNSELING INFORMATION

Severe Dermatologic Reactions

Advise patients about the signs and symptoms of serious skin manifestations. Instruct patients to stop taking FIRVANQ immediately and promptly seek medical attention at the first signs or symptoms of skin rash, mucosal lesions or blisters, [ see Warnings and Precautions (5.5) ].

Antibacterial Resistance

Patients should be counseled that antibacterial drugs including FIRVANQ should only be used to treat bacterial infections. They do not treat viral infections (e.g., the common cold). When FIRVANQ is prescribed to treat a bacterial infection, patients should be told that although it is common to feel better early in the course of therapy, the medication should be taken exactly as directed. Skipping doses or not completing the full course of therapy may (1) decrease the effectiveness of the immediate treatment and (2) increase the likelihood that bacteria will develop resistance and will not be treatable by FIRVANQ or other antibacterial drugs in the future.

Important Administration and Storage Instructions

Instruct the patient or caregiver to [ see Dosage and Administration (2.4) ]:

- Shake the reconstituted solutions of FIRVANQ well before each use and to use an oral dosing device that measures the appropriate volume of the oral solution in milliliters.
- Store the reconstituted solutions of FIRVANQ at refrigerated conditions, 2° C to 8° C (36° F to 46° F) when not in use.
- Discard reconstituted solutions of FIRVANQ after 14 days, or if it appears hazy or contains particulates.

FIRVANQ is a registered trademark of Azurity Pharmaceuticals, Inc.

Manufactured for:

Wilmington, MA 01887 USA

Patent: https://azurity.com/patents

This product's labeling may have been updated. For current Full Prescribing Information, please visit www.FIRVANQ.com

PN: 65628-0120
REV: 05

PRINCIPAL DISPLAY PANEL - 25 mg - 150 mL Carton Label

NDC 65628-204-05

Rx ONLY

FIRVANQ®
(vancomycin hydrochloride for oral solution)

FOR ORAL USE ONLY

Vancomycin 25 mg/mL Kit

EACH KIT INCLUDES:

- 1 bottle containing 3.84 g Vancomycin Hydrochloride USP, powder for oral solution,
  equivalent to 3.75 g Vancomycin
- 1 bottle conatining 147 mL Grape Flavored Diluentfor reconstitution

When reconstituted, each mL contains 25 mg Vancomycin

MUST BE
REFRIGERATED

azurity®
pharmaceuticals

150 mL
final volume after reconstitution

NDC 65628-204-05

Rx ONLY

TO THE PHARMACIST

STOP IMPORTANT:

- When reconstituted each mL contains 25 mg Vancomycin
- Add liquid contents of the Diluent bottle to the bottle containing
  Vancomycin Hydrochloride powder according to the preparation steps
  in the Full Prescribing Information
- Instruct patient to store reconstituted formulation at refrigerated temperature,
  2°-8°C (36°-46°F) [see USP]
- Discard 14 days after reconstitution or if the solution appears hazy

MANUFACTURED FOR:
azurity©
pharmaceuticals

WILMINGTON, MA 01887 USA

www.azurity.com

RECONSTITUTE
BEFORE DISPENSING

- For oral use only
- Avoid contact with eyes
- Keep container tightly closed
- Protect from light
- Protect from freezing
- Store kit at refrigerated
  temperature, 2°-8°C (36°-46°F)
  [see USP]

PRINCIPAL DISPLAY PANEL - 25 mg - 300 mL Carton Label

NDC 65628-205-10

Rx ONLY

FIRVANQ®
(vancomycin hydrochloride for oral solution)

FOR ORAL USE ONLY

Vancomycin 25 mg/mL Kit

EACH KIT INCLUDES:

- 1 bottle containing 7.7 g Vancomycin Hydrochloride USP, powder for oral solution,
  equivalent to 7.5 g Vancomycin
- 1 bottle conatining 295 mL Grape Flavored Diluentfor reconstitution

When reconstituted, each mL contains 25 mg Vancomycin

MUST BE
REFRIGERATED

azurity®
pharmaceuticals

300 mL
final volume after reconstitution

NDC 65628-205-10

Rx ONLY

TO THE PHARMACIST

STOP IMPORTANT:

- When reconstituted each mL contains 25 mg Vancomycin
- Add liquid contents of the Diluent bottle to the bottle containing
  Vancomycin Hydrochloride powder according to the preparation steps
  in the Full Prescribing Information
- Instruct patient to store reconstituted formulation at refrigerated temperature,
  2°-8°C (36°-46°F) [see USP]
- Discard 14 days after reconstitution or if the solution appears hazy

MANUFACTURED FOR:
azurity®
pharmaceuticals

WILMINGTON, MA 01887 USA

www.azurity.com

RECONSTITUTE
BEFORE DISPENSING

- For oral use only
- Avoid contact with eyes
- Keep container tightly closed
- Protect from light
- Protect from freezing
- Store kit at refrigerated
  temperature, 2°-8°C (36°-46°F)
  [see USP]

PRINCIPAL DISPLAY PANEL - 50 mg - 150 mL Carton Label

NDC 65628-206-05

Rx ONLY

FIRVANQ®
(vancomycin hydrochloride for oral solution)

FOR ORAL USE ONLY

Vancomycin 50 mg/mL Kit

EACH KIT INCLUDES:

- 1 bottle containing 7.7 g Vancomycin Hydrochloride USP, powder for oral solution,
  equivalent to 7.5 g Vancomycin
- 1 bottle conatining 145 mL Grape Flavored Diluentfor reconstitution

When reconstituted, each mL contains 50 mg Vancomycin

MUST BE
REFRIGERATED

azurity®
pharmaceuticals

150 mL
final volume after reconstitution

NDC 65628-206-05

Rx ONLY

TO THE PHARMACIST

STOP IMPORTANT:

- When reconstituted each mL contains 50 mg Vancomycin
- Add liquid contents of the Diluent bottle to the bottle containing
  Vancomycin Hydrochloride powder according to the preparation steps
  in the Full Prescribing Information
- Instruct patient to store reconstituted formulation at refigerated temperature,
  2°-8°C (36°-46°F) [see USP]
- Discard 14 days after reconstitution or if the solution appears hazy

MANUFACTURED FOR:
azurity©
pharmaceuticals

WILMINGTON, MA 01887 USA

www.azurity.com

RECONSTITUTE
BEFORE DISPENSING

- For oral use only
- Avoid contact with eyes
- Keep container tightly closed
- Protect from light
- Protect from freezing
- Store kit at refrigerated
  temperature, 2°-8°C (36°-46°F)
  [see USP]

PRINCIPAL DISPLAY PANEL - 50 mg - 300 mL Carton Label

NDC 65628-208-10

Rx ONLY

FIRVANQ®
(vancomycin hydrochloride for oral solution)

FOR ORAL USE ONLY

Vancomycin 50 mg/mL Kit

EACH KIT INCLUDES:

- 1 bottle containing 15.4 g Vancomycin Hydrochloride USP, powder for oral solution,
  equivalent to 15.0 g Vancomycin
- 1 bottle conatining 289 mL Grape Flavored Diluentfor reconstitution

When reconstituted, each mL contains 50 mg Vancomycin

MUST BE
REFRIGERATED

azurity®
pharmaceuticals

300 mL
final volume after reconstitution

NDC 65628-208-10

Rx ONLY

TO THE PHARMACIST

STOP IMPORTANT:

- When reconstituted each mL contains 50 mg Vancomycin
- Add liquid contents of the Diluent bottle to the bottle containing
  Vancomycin Hydrochloride powder according to the preparation steps
  in the Full Prescribing Information
- Instruct patient to store reconstituted formulation at refigerated temperature,
  2°-8°C (36°-46°F) [see USP]
- Discard 14 days after reconstitution or if the solution appears hazy

MANUFACTURED FOR:
azurity®
pharmaceuticals

WILMINGTON, MA 01887 USA

www.azurity.com

RECONSTITUTE
BEFORE DISPENSING

- For oral use only
- Avoid contact with eyes
- Keep container tightly closed
- Protect from light
- Protect from freezing
- Store kit at refrigerated
  temperature, 2°-8°C (36°-46°F)
  [see USP]